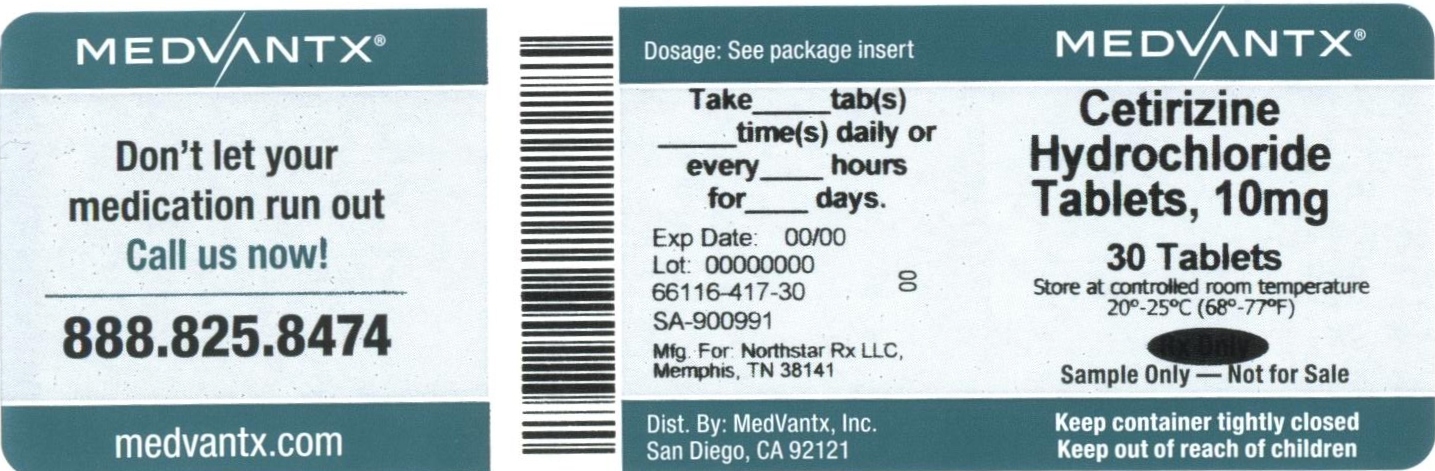 DRUG LABEL: CETIRIZINE HYDROCHLORIDE
NDC: 66116-417 | Form: TABLET, FILM COATED
Manufacturer: MedVantx, Inc.
Category: otc | Type: HUMAN OTC DRUG LABEL
Date: 20130527

ACTIVE INGREDIENTS: CETIRIZINE HYDROCHLORIDE 10 mg/1 1
INACTIVE INGREDIENTS: STARCH, CORN; LACTOSE MONOHYDRATE; POVIDONE K29/32; MAGNESIUM STEARATE

Active ingredient (in each tablet)

Cetirizine hydrochloride USP, 10 mg

Purpose

Antihistamine

Uses

temporarily relieves these symptoms due to hay fever or other upper respiratory allergies:

- runny nose
- sneezing
- itchy, watery eyes
- itching of the nose or throat

Warnings

Do not use if you have ever had an allergic reaction to this product or any of its ingredients or to an antihistamine containing hydroxyzine.

Ask a doctor before use if you have liver or kidney disease. Your doctor should determine if you need a different dose.

Ask a doctor or pharmacist before use if you are taking tranquilizers or sedatives.

When using this product

- drowsiness may occur
- avoid alcoholic drinks
- alcohol, sedatives, and tranquilizers may increase drowsiness
- be careful when driving a motor vehicle or operating machinery.

Stop use and ask a doctor if an allergic reaction to this product occurs. Seek medical help right away.

If pregnant or breast feeding:

if breast-feeding: not recommended

if pregnant: ask a health professional before use.

Keep out of reach of children. In case of overdose, get medical help or contact a Poison Control Center right away.

Directions

adults and children 6 years and over | one 10 mg tablet once daily; do not take more than one 10 mg tablet in 24 hours. A 5 mg product may be appropriate for less severe symptoms.
adults 65 years and over | ask a doctor
children under 6 years of age | ask a doctor
consumers with liver or kidney disease | ask a doctor

Other information

store between 20° to 25°C (68° to 77°F).

Inactive ingredients

corn starch, lactose monohydrate, povidone, magnesium stearate and opadry white. The components of opadry white are: hydroxypropyl methylcellulose, polyethylene glycol 400, titanium dioxide

Questions or comments?

call toll free 1-800-206-7821

PACKAGE LABEL.PRINCIPAL DISPLAY PANEL

NDC 16714-271-02

Cetirizine Hydrochloride Tablets, USP 10 mg

6 Years and Older

Allergy

Antihistamine

24 Hour Relief of

- runny nose
- sneezing
- itchy, watery eyes
- itching of the nose or throat

NORTHSTAR

100 Tablets